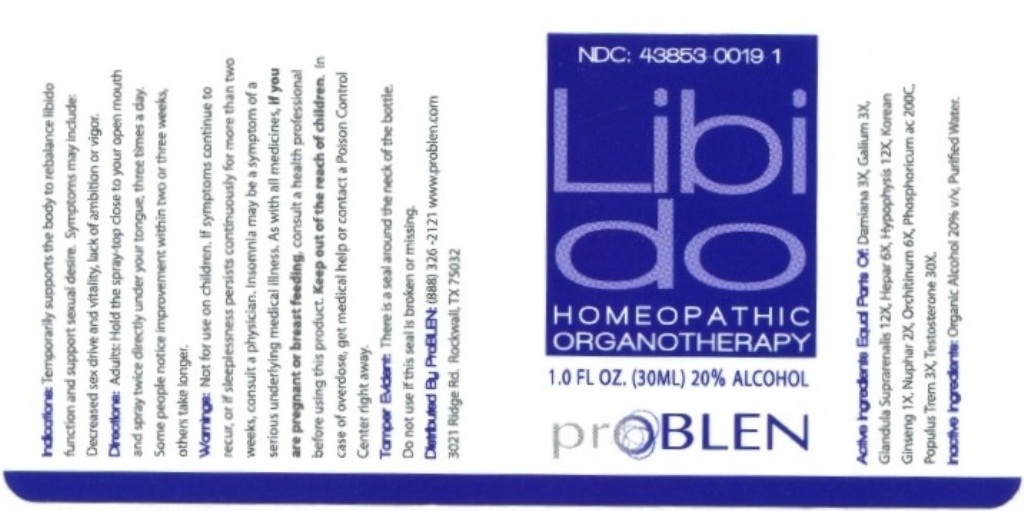 DRUG LABEL: Libido
NDC: 43853-0019 | Form: LIQUID
Manufacturer: ProBlen
Category: homeopathic | Type: HUMAN OTC DRUG LABEL
Date: 20210115
DEA Schedule: CIII

ACTIVE INGREDIENTS: GALIUM APARINE 3 [hp_X]/30 mL; SUS SCROFA ADRENAL GLAND 12 [hp_X]/30 mL; PORK LIVER 6 [hp_X]/30 mL; SUS SCROFA PITUITARY GLAND 12 [hp_X]/30 mL; ASIAN GINSENG 1 [hp_X]/30 mL; NUPHAR LUTEA ROOT 2 [hp_X]/30 mL; SUS SCROFA TESTICLE 6 [hp_X]/30 mL; PHOSPHORIC ACID 200 [hp_C]/30 mL; POPULUS TREMULOIDES WHOLE 3 [hp_X]/30 mL; TESTOSTERONE 30 [hp_X]/30 mL; TURNERA DIFFUSA LEAFY TWIG 3 [hp_X]/30 mL
INACTIVE INGREDIENTS: ALCOHOL; WATER

ProBlen Libido

ACTIVE INGREDIENT

Active Ingredients Equal Parts Of: Damiana 3X, Galium 3X, Glandula Suprarenalis 12X, Hepar 6X, Hypophysis 12X, Korean Ginseng 1X, Nuphar 2X, Orchitinum 6X, Phosphoricum ac 200C, Populus Trem 3X, Testosterone 30X.

INDICATIONS AND USAGE

Indications: Temporarily supports the body to rebalance libido function and support sexual desire. Symptoms may include: Decreased sex drive and vitality, lack of ambition or vigor.

WARNINGS

Warnings: Not for use on children. If symptoms continue to recur, or if sleeplessness persists continuously for more than two weeks, consult a physician. Insomnia may be a symptom of a serious underlying medical illness. As with all medicines, if you are pregnant or breastfeeding, consult a health professional before using this product. In case of overdose, get medical help or contact a Poison Control Center right away.

- Keep out of reach of children.

DOSAGE AND ADMINISTRATION

Directions: Adults: Hold the spray-top close to your open mouth and spray twice directly under your tongue, three times a day. Some people notice improvement within two or three weeks, others take longer.

OTHER SAFETY INFORMATION

Tamper Evident: There is a seal around the neck of the bottle. Do not use if seal is broken or missing.

INACTIVE INGREDIENT

Inactive Ingredients: Organic Alcohol 20% v/v, Purified Water

QUESTIONS

Distributed By ProBlen: (888) 326-2121 www. problen.com
3021 Ridge Rd. Rockwall, TX 75032

PACKAGE LABEL

NDC: 43853-0019-1

LIBIDO

HOMEOPATHIC ORGANOTHERAPY

1.0 FL OZ. (30ML) 20% ALCOHOL

ProBLEN

PURPOSE

Temporarily supports the body to rebalance libido function and support sexual desire.